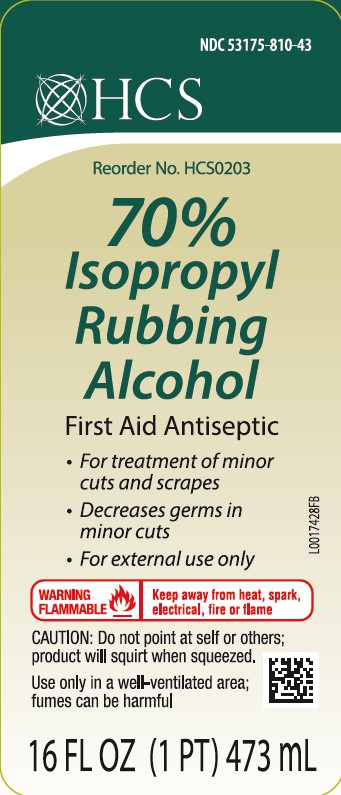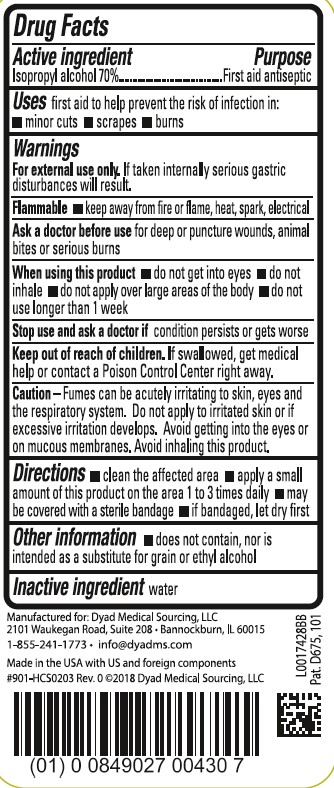 DRUG LABEL: Isopropyl Alcohol
NDC: 53175-810 | Form: LIQUID
Manufacturer: Dyad Medical Sourcing, LLC
Category: otc | Type: HUMAN OTC DRUG LABEL
Date: 20260204

ACTIVE INGREDIENTS: ISOPROPYL ALCOHOL 70 mL/100 mL
INACTIVE INGREDIENTS: WATER

HCS (Dyad - Old) 452.000/810AA
70% Isopropyl Alcohol

Active Ingredient

Isopropyl alcohol 70%

Purpose

First aid antiseptic

Use

First aid to help prevent the risk of infection in:

- minor cuts
- scrapes
- burns

Warnings

For external use only. If taken internally serious gastric disturbances will result.

Flammable Keep away from fire or flame, heat, spark, electrical

Ask a doctor before use

for deep or puncture wounds, animal bites or serious burns

When using this product

- do not get into eyes
- do not inhale
- do not apply over large areas of the body
- do not use longer than 1 week

Stop use and ask a doctor if

condition persists or gets worse

Keep out of reach of children.

If swallowed, get medical help or contact a Poison Control Center right away.

Caution

Fumes can be acutely irritating to skin, eyes and the respiratory system. Do not apply to irritated skin or if excessive irritation develops. Avoid getting into the eyes or on mucous membranes. Avoid inhaling this product.

Directions

- clean the affected area
- apply a small amount of this product on the area 1 to 3 times daily
- may be covered with a sterile bandage
- if bandaged, let dry first

Other information

- does not contain, nor is intended as a substitute for grain or ethyl alcohol

Inactive ingredient

water

ADVERSE REACTION

Manufactured for: Dyad Medical Sourcing, LLC

2101 Waukegan Road, Suite 208, Bannokburn, IL 60015

1-855-241-1773, info@dyadms.com

Made in the USA with US and foreign components

#901-HCS0203 Rev. 0 2018 Dyad Medical Sourcing, LLC

Pat. D675, 101

principal display panel

NDC 53175-810-43

HCS

Reorder NO HCS0203

70%

Isopropyl

Rubbing

Alcohol

First Aid Antiseptic

- For treatment of minor cuts and scrapes
- Decreases germs in minor cuts
- For external use only

WARNING FLAMMABLE - Keep away from heat, spark, electrical, fire or flame

CAUTION: Do not point at self or others; product will squirt when squeezed.

Use only in well-ventilated area; fumes can be harmful

16 FL OZ (1PT) 473 mL